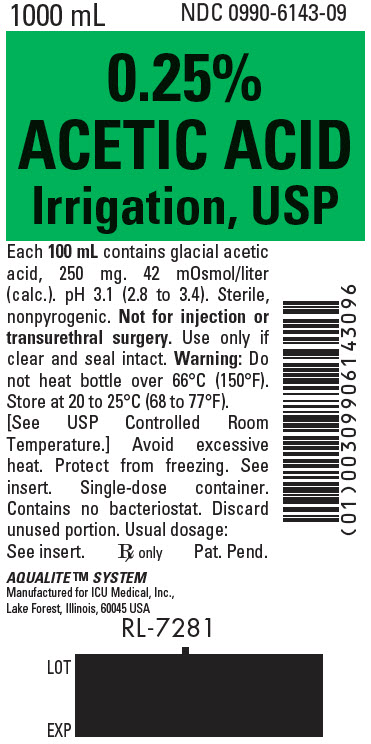 DRUG LABEL: Acetic Acid
NDC: 0990-6143 | Form: IRRIGANT
Manufacturer: ICU Medical Inc.
Category: prescription | Type: HUMAN PRESCRIPTION DRUG LABEL
Date: 20200617

ACTIVE INGREDIENTS: ACETIC ACID 250 mg/100 mL
INACTIVE INGREDIENTS: WATER

0.25% ACETIC ACID IRRIGATION, USP

UROLOGIC IRRIGATING FLUID FOR PATIENTS REQUIRING PROLONGED INDWELLING URETHRAL CATHETERIZATION...NOT FOR TRANSURETHRAL SURGICAL PROCEDURES.

Not For Injection By Usual Parenteral Routes

Semi-Rigid Irrigation Container

Rx only

DESCRIPTION

0.25% Acetic Acid Irrigation, USP, is a sterile, nonpyrogenic aqueous solution of Glacial Acetic Acid, USP for irrigation of the urinary bladder by the transurethral route (NOT FOR TUR). Each 100 mL contains 250 mg of Glacial Acetic Acid, in water for injection.

The solution is hypotonic, 42 mOsmol/liter (calc.), in relation to the extracellular fluid compartment of the body (280 mOsmol/liter) and has a pH of 3.1 (2.8 to 3.4).

Other than the active ingredient, acetic acid, the solution contains no bacteriostat, antimicrobial agent or added buffer and is intended only for use as a single-dose irrigation. When smaller volumes are required the unused portion should be discarded.

The solution is a urinary bladder antimicrobial, acidifying irrigant.

Glacial Acetic Acid, USP is chemically designated acetic acid (C2H4O2) a liquid miscible with water. It has the following structural formula:

CH3COOH

Water for Injection is chemically designated H2O.

The semi-rigid container is fabricated from a specially formulated polyolefin. It is a copolymer of ethylene and propylene. The container requires no vapor barrier to maintain the proper drug concentration.

Solutions in contact with the plastic container may leach out certain chemical components from the plastic in very small amounts; however, biological testing was supportive of the safety of the plastic container materials.

Exposure to temperatures above 25°C/77°F during transport and storage will lead to minor losses in moisture content. Higher temperatures lead to greater losses. It is unlikely that these minor losses will lead to clinically significant changes within the expiration period.

CLINICAL PHARMACOLOGY

Irrigation of the urinary bladder with acetic acid solution in a concentration of 0.25% has been shown to exert an antimicrobial action against a variety of microorganisms (especially ammonia-forming bacteria) that frequently gain access to the urinary bladder in patients who require prolonged indwelling urethral catheterization. Its antimicrobial action is dependent on administration via the indwelling catheter at a sufficient rate (continuous or intermittent) to maintain an effluent pH of at least 5.0. Maintenance of low pH of bladder urine also helps reduce formation of calcium encrustations in the indwelling catheter.

INDICATIONS AND USAGE

0.25% Acetic Acid Irrigation, USP is indicated as a constant or intermittent bladder rinse to help prevent the growth and proliferation of susceptible urinary pathogens (especially ammonia-forming bacteria) in the management of patients who require prolonged placement of an indwelling urethral catheter. It also may be used for periodic irrigation of an indwelling catheter to help maintain patency by reducing the formation of calcium encrustations.

CONTRAINDICATIONS

NOT FOR INJECTION BY USUAL PARENTERAL ROUTES.

This solution is contraindicated for irrigation during transurethral surgical procedures.

WARNINGS

FOR IRRIGATION ONLY. NOT FOR INJECTION.

1. Use of this solution in patients with mucosal lesions of the urinary bladder may be harmful due to irritation of the lesions. Absorption via open lesions of the bladder mucosa may result in systemic acidosis.
2. The contents of an opened container should be used promptly to minimize the possibility of bacterial growth or pyrogen formation.
3. Discard the unused portion of irrigating solution since it contains no preservative.
4. Do not heat over 66°C (150°F).

PRECAUTIONS

If pain or hematuria should occur during irrigation, it should be discontinued and the patient re-evaluated.

Do not use unless solution is clear, seal is intact and container is undamaged. Discard unused portion.

Carcinogenesis, Mutagenesis, Impairment of Fertility: Studies with Acetic Acid Irrigation, USP have not been performed to evaluate carcinogenic potential, mutagenic potential, or effects on fertility.

Nursing Mothers: Caution should be exercised when Acetic Acid Irrigation, USP is administered to a nursing woman.

Pregnancy: Teratogenic Effects. Pregnancy Category C. Animal reproduction studies have not been conducted with Acetic Acid Irrigation, USP. It is also not known whether Acetic Acid Irrigation, USP can cause fetal harm when administered to a pregnant woman or can affect reproduction capacity. Acetic Acid Irrigation, USP should be given to a pregnant woman only if clearly needed.

Pediatric Usage: The safety and effectiveness have not been established. Its limited use in pediatric patients has been inadequate to fully define proper dosage and limitations for use.

ADVERSE REACTIONS

Systemic acidosis has been reported in patients receiving urinary bladder irrigation with 0.25% acetic acid solution. Urologic pain and hematuria have been reported in patients receiving urinary bladder irrigation with 0.25% acetic acid solution.

OVERDOSAGE

Systemic absorption is unlikely unless there are open lesions of the bladder mucosa that have gone undetected. In such event, discontinue the irrigation, evaluate the patient for possible systemic acidosis, intravascular hemolysis and circulatory overload and institute appropriate countermeasures as indicated. See WARNINGS, PRECAUTIONS and ADVERSE REACTIONS.

Oral LD50 in mice: 5 g/kg.

DOSAGE AND ADMINISTRATION

0.25% Acetic Acid Irrigation, USP may be administered by gravity drip via an administration set connected to an indwelling urethral catheter designed for continuous or intermittent two-way flow. A disposable dispensing set should be used. A bulb or piston syringe may be used for periodic irrigation of an indwelling catheter.

For continuous or intermittent irrigation, the rate of administration will correspond roughly to the rate of urine flow and should be adjusted to maintain a urinary effluent pH of 4.5 to 5.0. Nitrazine or other pH paper may be used to monitor pH, preferably at least four times daily. Drip rate should be adjusted as necessary to maintain desired pH; increasing flow rate reduces pH value and vice versa. With continuous or intermittent irrigation, each patient will require a volume of approximately 500 to 1500 mL per 24 hours.

For periodic irrigation of an indwelling catheter to maintain patency, about 50 mL is required for each irrigation and may be administered using a bulb or piston syringe for injection and aspiration as often as desired.

Parenteral drug products should be inspected visually for particulate matter and discoloration prior to administration, whenever solution and container permit. See PRECAUTIONS.

HOW SUPPLIED

0.25% Acetic Acid Irrigation, USP is supplied in single-dose irrigation containers as follows:

List | Container | Size (mL)
6143 | Semi-rigid | 250 & 1000

Exposure of pharmaceutical products to heat should be minimized. Avoid excessive heat. Protect from freezing. Store at 20 to 25°C (68 to 77°F). [See USP Controlled Room Temperature.]

Revised: December, 2018

EN-5788

Manufactured for ICU Medical, Inc., Lake Forest, Illinois, 60045, USA

PRINCIPAL DISPLAY PANEL - 1000 mL Bottle Label

1000 mL
NDC 0990-6143-09

0.25%
ACETIC ACID
Irrigation, USP

Each 100 mL contains glacial acetic
acid, 250 mg. 42 mOsmol/liter
(calc.). pH 3.1 (2.8 to 3.4). Sterile,
nonpyrogenic. Not for injection or
transurethral surgery. Use only if
clear and seal intact. Warning: Do
not heat bottle over 66°C (150°F).
Store at 20 to 25°C (68 to 77°F).
[See USP Controlled Room
Temperature.] Avoid excessive
heat. Protect from freezing. See
insert. Single-dose container.
Contains no bacteriostat. Discard
unused portion. Usual dosage:
See insert.
Rx only
Pat. Pend.

AQUALITE™ SYSTEM
Manufactured for ICU Medical, Inc.,
Lake Forest, Illinois, 60045 USA

RL-7281

LOT

EXP